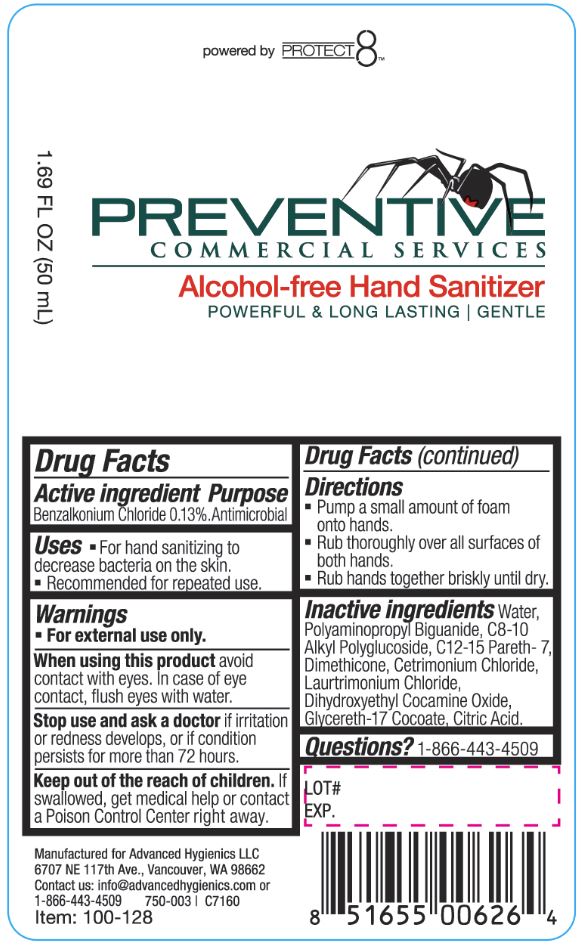 DRUG LABEL: Alcohol free Hand Sanitizer
NDC: 63002-005 | Form: LIQUID
Manufacturer: Advanced Hygienics LLC
Category: otc | Type: HUMAN OTC DRUG LABEL
Date: 20190311

ACTIVE INGREDIENTS: BENZALKONIUM CHLORIDE 0.13 g/100 mL
INACTIVE INGREDIENTS: Water; POLIHEXANIDE; CAPRYLYL GLUCOSIDE; C12-15 PARETH-7; DIMETHICONE; CETRIMONIUM CHLORIDE; LAURTRIMONIUM CHLORIDE; DIHYDROXYETHYL COCAMINE OXIDE; GLYCERETH-17 COCOATE; CITRIC ACID MONOHYDRATE

Drug Facts

Active ingredient

Benzalkonium Chloride 0.13%.

Purpose

Antimicrobial

Uses

For hand sanitizing to decrease bacteria on the skin.

Recommended for repeated use.

Warnings

For external use only.

When using this product avoid contact with eyes.

In case of eye contact, flush eyes with water.

Stop use and ask a doctor if irritation or redness develops, or if condition persists for more than 72 hours.

Keep out of the reach of children.

If swallowed, get medical help or contact a Poison Control Center right away.

Directions

Pump a small amount of foam onto hands.

Rub thoroughly over all surfaces of both hands.

Rub hands together briskly until dry.

Inactive ingredients

Water, Polyaminopropyl Biguanide, C8-10 Alkyl Polyglucoside, C12-15 Pareth-7, Dimethicone, Cetrimonium Chloride, Laurtrimonium Chloride, Dihydroxyethyl Cocamine Oxide, Glycereth-17 Cocoate, Citric Acid.

PACKAGE LABEL

powered by PROTECT 8

PREVENTATIVE

COMMERCIAL SERVICES

Alcohol-free Hand Sanitizer

Powerful and Long Lasting I Gentle

1.69 FL OZ (50 mL)